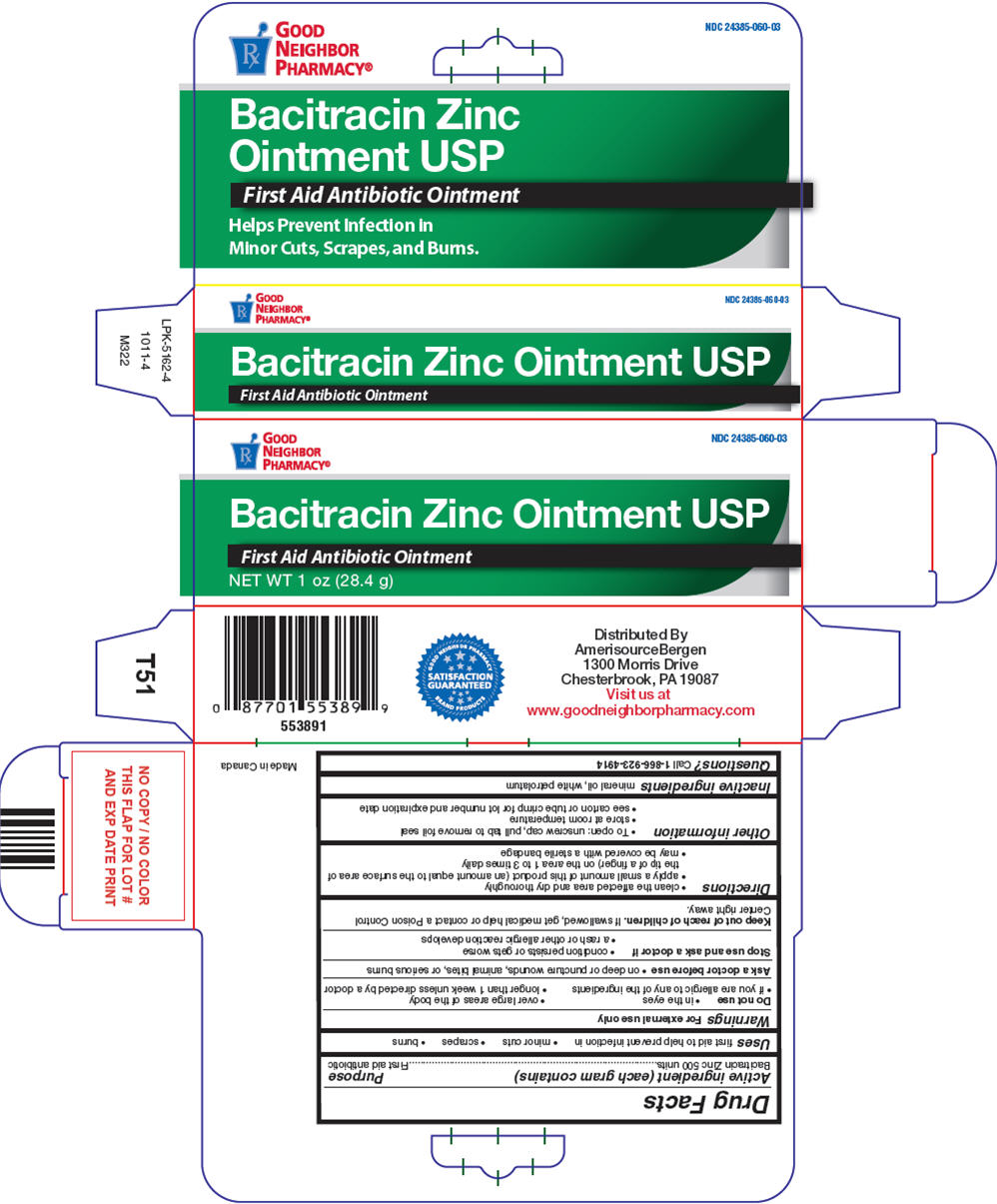 DRUG LABEL: Good Neighbor Pharmacy

NDC: 24385-060 | Form: OINTMENT
Manufacturer: AmerisourceBergen
Category: otc | Type: HUMAN OTC DRUG LABEL
Date: 20250711

ACTIVE INGREDIENTS: BACITRACIN ZINC 500 [iU]/1 g
INACTIVE INGREDIENTS: MINERAL OIL; PETROLATUM

Good Neighbor Pharmacy®
Bacitracin Zinc

Drug Facts

Active ingredient (each gram contains)

Bacitracin Zinc 500 units

Purpose

First aid antibiotic

Uses

first aid to help prevent infection in

- minor cuts
- scrapes
- burns

Warnings

For external use only

Do not use

- in the eyes
- over large areas of the body
- if you are allergic to any of the ingredients
- longer than 1 week unless directed by a doctor

Ask a doctor before use

- on deep or puncture wounds, animal bites, or serious burns

Stop use and ask a doctor if

- condition persists or gets worse
- a rash or other allergic reaction develops

Keep out of reach of children.If swallowed, get medical help or contact a Poison Control Center right away.

Directions

- clean the affected area and dry thoroughly
- apply a small amount of this product (an amount equal to the surface area of the tip of a finger) on the area 1 to 3 times daily
- may be covered with a sterile bandage

Other information

- To open: unscrew cap, pull tab to remove foil seal
- store at room temperature
- see carton or tube crimp for lot number and expiration date

Inactive ingredients

mineral oil, white petrolatum

Questions?

Call 1-866-923-4914

Distributed By
AmerisourceBergen
1300 Morris Drive
Chesterbrook, PA 19087

PRINCIPAL DISPLAY PANEL - 28.4 g Tube Carton

NDC 24385-060-03

Rx
GOOD
NEIGHBOR
PHARMACY ®

Bacitracin Zinc Ointment USP

First Aid Antibiotic Ointment

NET WT 1 oz (28.4 g)